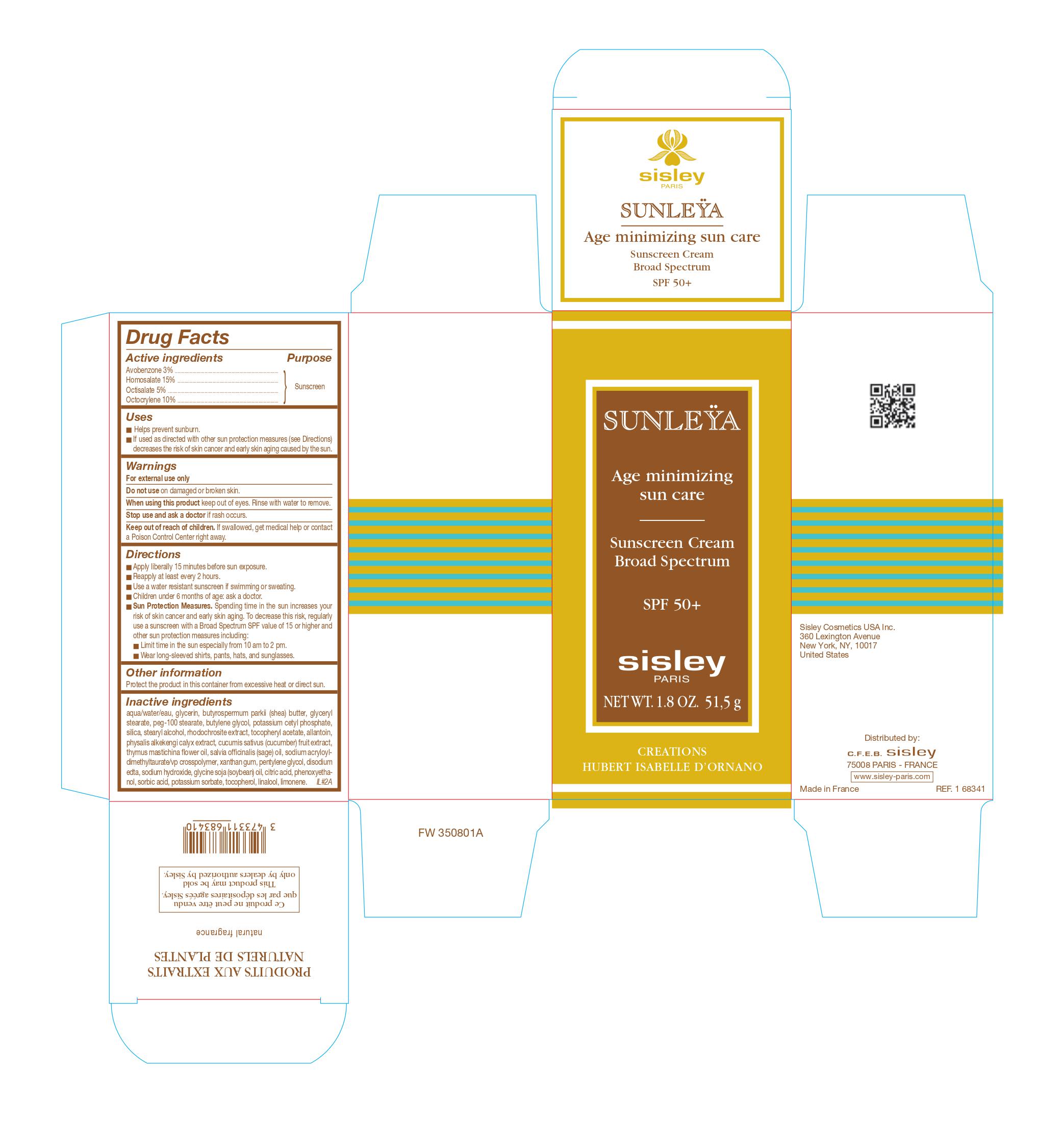 DRUG LABEL: 
                  SUNLEYA Age minimizing sun care

                
                  

NDC: 66097-003 | Form: CREAM
Manufacturer: C.F.E.B. Sisley
Category: otc | Type: HUMAN OTC DRUG LABEL
Date: 20241210

ACTIVE INGREDIENTS: AVOBENZONE 30 mg/1 g; HOMOSALATE 150 mg/1 g; OCTISALATE 50 mg/1 g; OCTOCRYLENE 100 mg/1 g
INACTIVE INGREDIENTS: WATER; GLYCERIN; SHEANUT OIL; GLYCERYL MONOSTEARATE; PEG-100 STEARATE; BUTYLENE GLYCOL; POTASSIUM CETYL PHOSPHATE; SILICON DIOXIDE; STEARYL ALCOHOL; .ALPHA.-TOCOPHEROL ACETATE; ALLANTOIN; PHYSALIS ALKEKENGI CALYX; CUCUMBER; MANGANESE CARBONATE; SODIUM ACRYLOYLDIMETHYLTAURATE; XANTHAN GUM; PENTYLENE GLYCOL; EDETATE DISODIUM; SODIUM HYDROXIDE; CITRIC ACID MONOHYDRATE; THYMUS MASTICHINA FLOWERING TOP OIL; SAGE OIL; PHENOXYETHANOL; SORBIC ACID; POTASSIUM SORBATE; LINALOOL, (+/-)-

SUNLEYA Age minimizing sun care SPF 50 plus

Active ingredients

Avobenzone 3 % Octinoxate 5 % Octisalate 5 % Oxybenzone 4 %

Purpose

Sunscreen

Uses

- Helps prevent sunburn
- If used as directed with other sun protection measures (see Directions) decreases the risk of skin cancer and early skin aging caused by the sun.

Warnings

For external use only

Do not use

on damaged or broken skin.

When using this product

keep out of eyes. Rinse with water to remove.

Stop use and ask a doctor

if rash occurs.

Keep out of reach of children.

If swallowed, get medical help or contact a Poison Control Center right away.

Directions

- Apply liberally 15 minutes before sun exposure.
- Reapply at least every 2 hours.
- Use a water resistant sunscreen if swimming or sweating.
- Children under 6 months of age: ask a doctor.
- Spending time in the sun increases your risk of skin cancer and early skin aging. To decrease this risk, regularly use a sunscreen with a Broad Spectrum SPF value of 15 or higher and other sun protection measures including: Sun Protection Measures:
- Limit time in the sun especially from 10 am to 2 pm.
- Wear long-sleeved shirts, pants, hats, and sunglasses.

Other information

Protect the product in this container from excessive heat or direct sun.

Inactive ingredients

water, glycerin, butyrospermum parkii (shea butter), glyceryl stearate, peg-100 stearate, butylene glycol, potassium cetyl phosphate, silica, stearyl alcohol, tocopherol acetate, allantoin, physalis alkekengi calyx extract, cucumis sativus (cucumber) fruit extract, rhodochrosite extract, sodium acryloyldimethyltaurate/vp crosspolymer, xanthan gum, pentylene glycol, disodium edta, sodium hydroxide, citric acid, thymus mastichina flower oil, salvia officinalis (sage) oil, phenoxyethanol, phenoxyethanol, sorbic acid, potassium sorbate, linalool, limonene

PACKAGE LABEL

SUNLEYA Age minimizing sun care Sunscreen Cream Broad Spectrum SPF 50+ sisley PARIS NET WT. 1.8 OZ. 51,5 g CREATIONS HUBERT ISABELLE D'ORNANO Sisley USA 7 Renaissance Square, 3rd Floor, White Plains, NY 10601